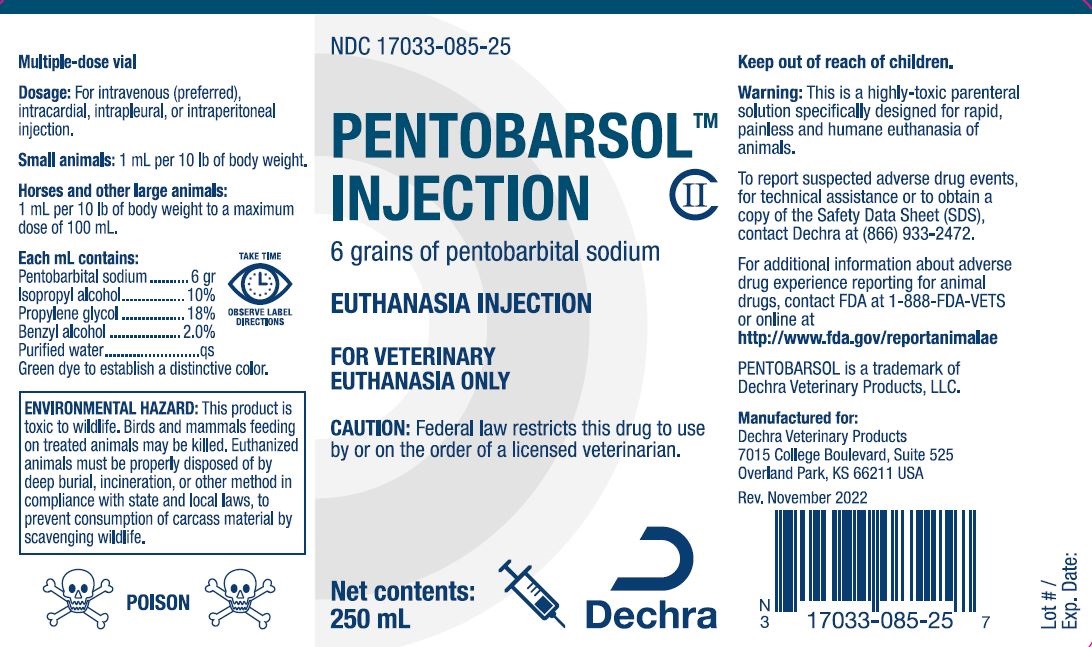 DRUG LABEL: Pentobarsol
NDC: 17033-085 | Form: INJECTION, SOLUTION
Manufacturer: Dechra Veterinary Products, LLC
Category: animal | Type: PRESCRIPTION ANIMAL DRUG LABEL
Date: 20230111
DEA Schedule: CII

ACTIVE INGREDIENTS: PENTOBARBITAL SODIUM 390 mg/1 mL
INACTIVE INGREDIENTS: ISOPROPYL ALCOHOL 0.10 mL/1 mL; PROPYLENE GLYCOL 0.180 mL/1 mL; BENZYL ALCOHOL 0.02 mL/1 mL; WATER 0.01 mL/1 mL

Pentobarsol Injection

DESCRIPTION:

Pentobarsol (euthanasia) Injection

NDC 17033-085-25

FOR VETERINARY EUTHANASIA ONLY. Keep Out of Reach of Children.

CAUTION: Federal law restricts this drug to use by or on the order of a licensed veterinarian.

6 grains of pentobarbital sodium

Net contents: 250 mL

DOSAGE AND ADMINISTRATION:

Mulitple Dose Vial

Dosage: For intravenous (preferred), intracardial, intrapleural, or intraperitoneal injection.

Small Animals: Inject rapidly 1 mL per 10 lbs. of bady weight. Minimum dose 1 mL.

Horses and other Large Animals: Inject rapidly 1 mL per 10 lbs. of obdy weight, to a maximum of 100 mL.

Each mL contains:

Pentobarbital sodium ..... 6 gr.

Isopropyl alcohol .......... 10%

Propylene glycol ........... 18%

Benzyl alcohol .............. 2.0%

Purified water ............... qs

Green dye to establish a distinctive color.

TAKE TIME - OBSERVE LABEL DIRECTIONS

WARNING:

This is a highly toxic parenteral solution specifically designed for rapid, painless, and humane euthanasia of animals.

ENVIRONMENTAL HAZARD:

This product is toxic to wildlife. Birds and mammals feeding on treated animals may be killed. Euthanized animals must be properly disposed of by deep burial, incineration, or other method in compliance with state and local laws to prevent consumption of carcass material by scavenging wildlife.

ADVERSE REACTIONS

To report suspected adverse drug events, for technical assistance, or to obtain a copy of the Safety Data Sheet (SDS), contact Dechra at (866) 933-2472. For additional information about adverse drug experience reporting for animals, contact FDA at 1-888-FDA-VETS or online at http://www.fda.gov/reportanimalae.

PENTOBARSOL is a trademark of Dechra Vetrinary Products, LLC.

Manufactured for:

Dechra Veterinary Products
7015 College Boulevard, Suite 525
Overland Park, KS 66211

Rev.: 01/2023